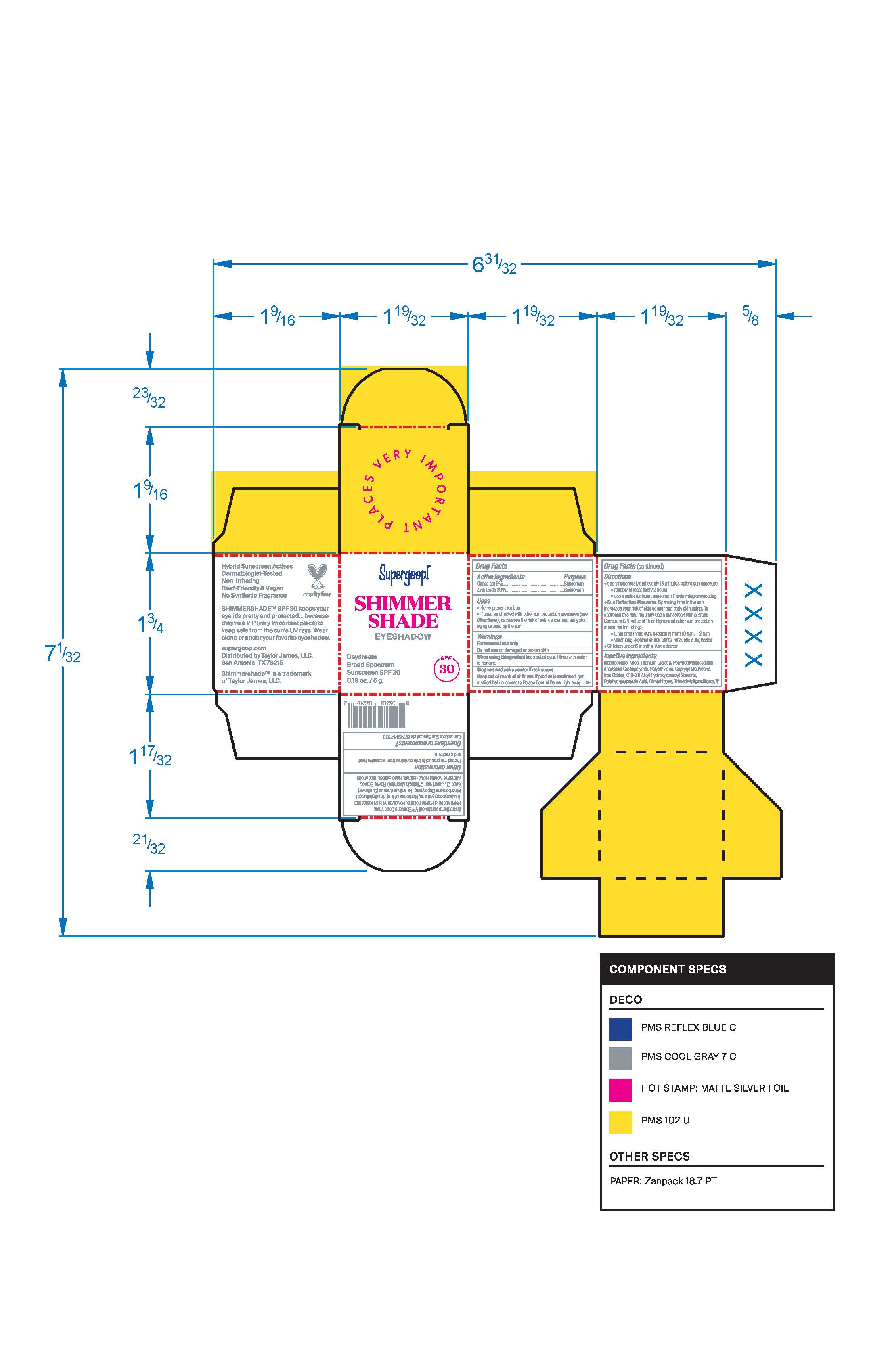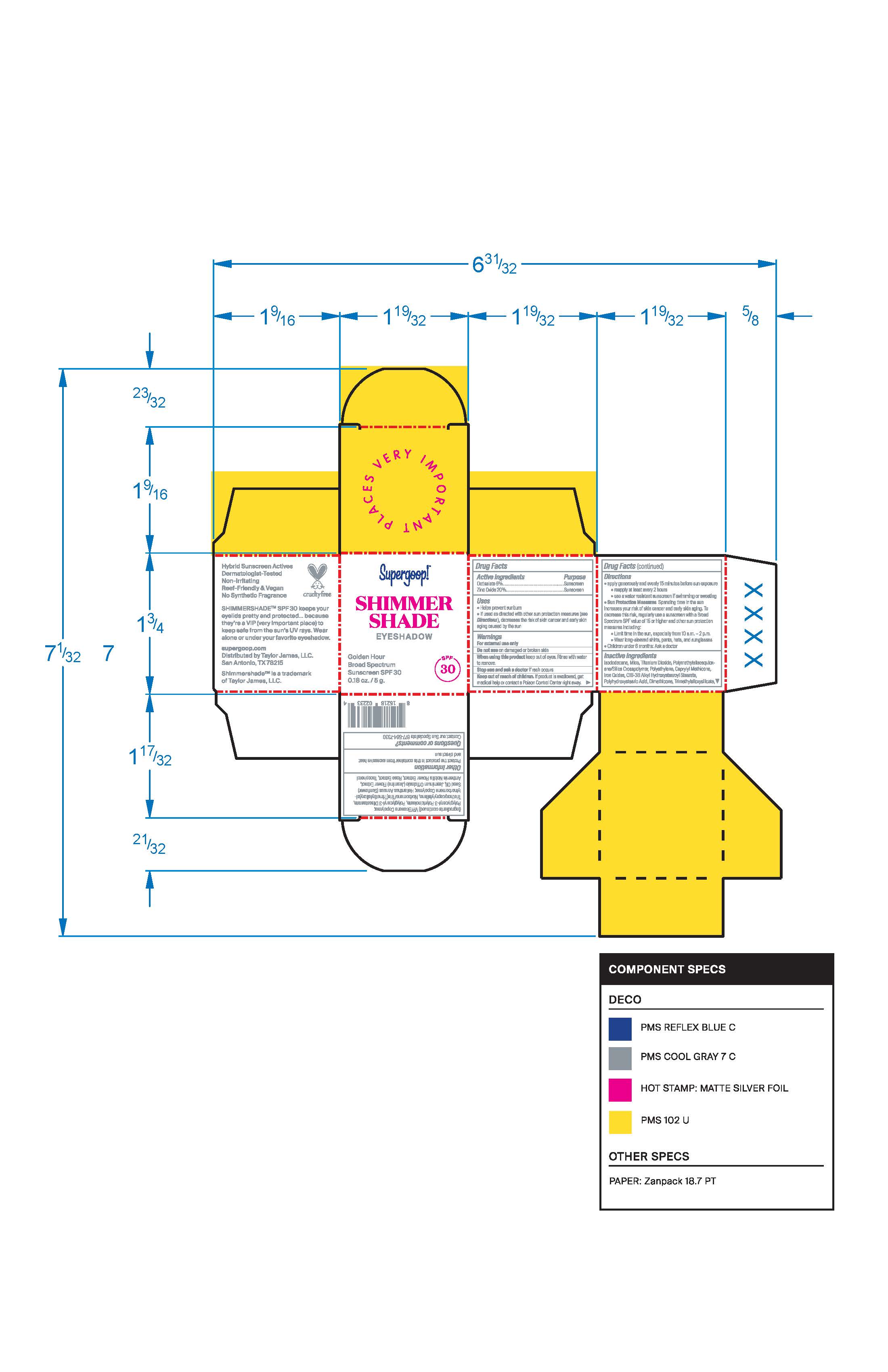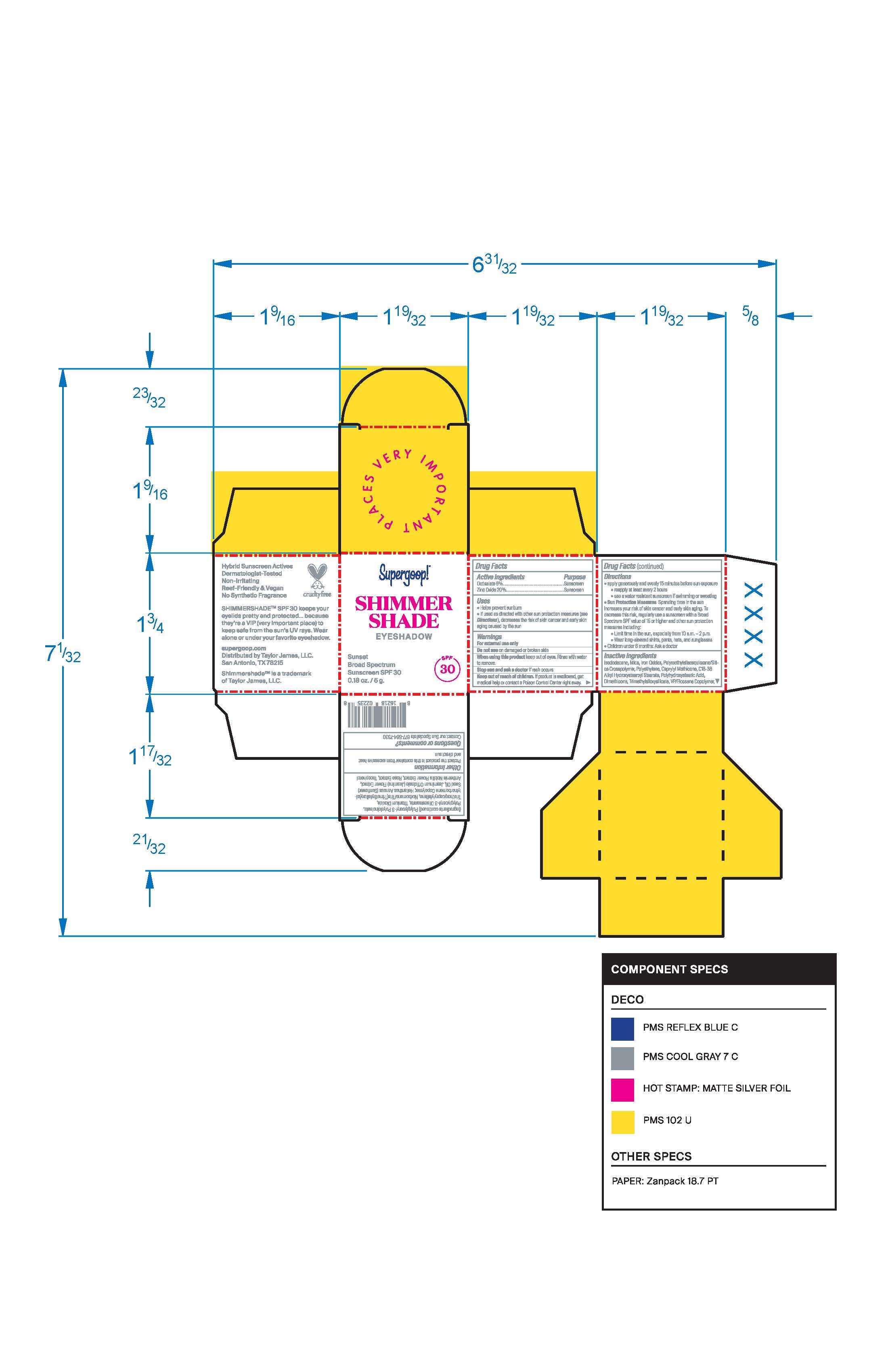 DRUG LABEL: Shimmershade Broad Spectrum Sunscreen SPF 30 Golden Hour
NDC: 75936-302 | Form: CREAM
Manufacturer: Supergoop, LLC
Category: otc | Type: HUMAN OTC DRUG LABEL
Date: 20241204

ACTIVE INGREDIENTS: OCTISALATE 5 g/100 g; ZINC OXIDE 20 g/100 g
INACTIVE INGREDIENTS: MICA; TITANIUM DIOXIDE; JASMINUM OFFICINALE FLOWER; HIGH DENSITY POLYETHYLENE; TRIETHOXYCAPRYLYLSILANE; POLYHYDROXYSTEARIC ACID (2300 MW); FERRIC OXIDE RED; ISODODECANE; CHAMAEMELUM NOBILE FLOWER; SILICON DIOXIDE; TRIMETHYLSILOXYSILICATE (M/Q 0.8-1.0); VINYLPYRROLIDONE/EICOSENE COPOLYMER; .DELTA.-TOCOPHEROL; CAPRYLYL TRISILOXANE; SUNFLOWER OIL; POLYGLYCERYL-3 DIISOSTEARATE; DIMETHICONE

Shimmershade Broad Spectrum SPF 30 Golden Hour

Active Ingredients Purpose

Octisalate 5% Sunscreen

Zinc Oxide 20% Sunscreen

Uses

- Helps prevent sunburn
- If used as directed with other sun protection measures (see Directions), decreases the risk of skin cancer and early skin aging caused by the sun

Keep out of reach of children. If product is swallowed, get medical help or contact a Poison Control Center right away.

Stop use and ask a doctor if rash occurs.

Warnings

For external use only

Do not use on damaged or broken skin.

When using this product keep out of eyes. Rinse with water to remove.

Directions

apply generously and evenly 15 minutes before sun exposure
reapply at least every 2 hours
Sun Protection Measures Spending time in the sun increases your risk of skin cancer and early skin aging. To decrease this risk, regularly use a sunscreen with a Broad Spectrum SPF value of 15 or higher and other sun protection and other sun protection measures including:
Limit time in the sun, especially from 10 a.m.- 2 p.m.
Wear long sleeved shirts, pants, hats, and sunglasses
Children under 6 months: Ask a doctor

Inactive Ingredients

Isododecane, Mica, Titanium Dioxide, Polymethylsilsesquioxane/Silica Crosspolymer, Polyethylene,
Caprylyl Methicone, Iron oxides, C18-38 Alkyl Hydroxystearoyl Stearate, Polyhydroxystearic Acid,
Dimethicone, Trimethylsiloxysilicate, Silica, VP/Eicosene Copolymer, Polyglyceryl-3 Polyricinoleate,
Polyglyceryl-3 Diisostearate,Triethoxycaprylylsilane, Norbornene/tris(trimethylsiloxy)silyl-norbornene
Copolymer, Tin Oxide, Helianthuus Annuus (Sunflower) Seed Oil, Jasminum Officinale (Jasmine) Flower
Extract, Rose Extract, Tocopherol.

PACKAGE LABEL

Shimmershade

Broad Spectrum SPF 30

Golden Hour

Supergoop

0.18 oz./5 g

Shimmershade

Broad Spectrum SPF 30

Sunset

Supergoop

0.18 oz./5 g

Shimmershade

Broad Spectrum SPF 30

Daydream

Supergoop

0.18 oz./5 g